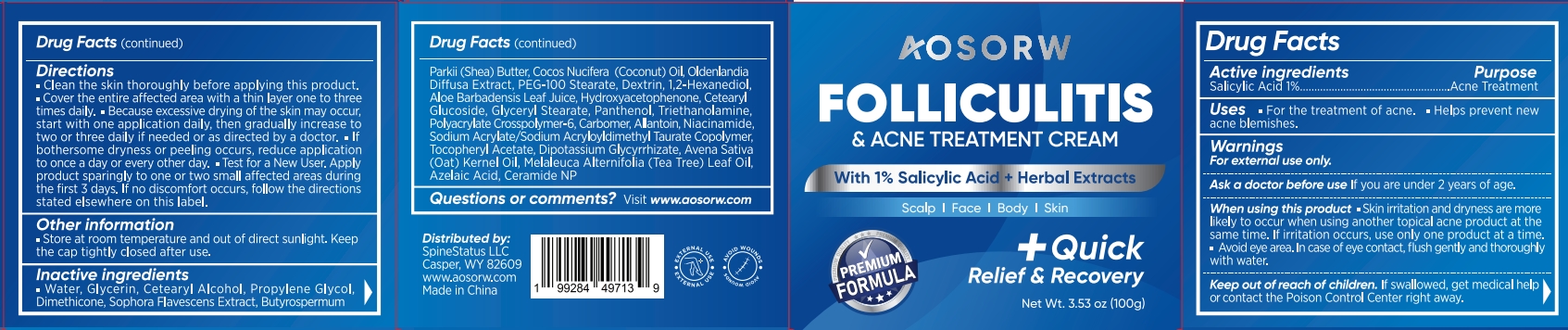 DRUG LABEL: AOSORW Folliculitis and Acne Treatment Cream
NDC: 85498-012 | Form: CREAM
Manufacturer: SpineStatus LLC
Category: otc | Type: HUMAN OTC DRUG LABEL
Date: 20251103

ACTIVE INGREDIENTS: SALICYLIC ACID 1 g/100 g
INACTIVE INGREDIENTS: BUTYROSPERMUM PARKII (SHEA) BUTTER; CETEARYL GLUCOSIDE; AVENA SATIVA (OAT) KERNEL OIL; GLYCERIN; ALOE BARBADENSIS LEAF JUICE; MELALEUCA ALTERNIFOLIA (TEA TREE) LEAF OIL; WATER; DIMETHICONE; CERAMIDE NP; .ALPHA.-TOCOPHEROL ACETATE; TRIETHANOLAMINE; POLYACRYLATE CROSSPOLYMER-6; DEXTRIN, CORN; NIACINAMIDE; DIPOTASSIUM GLYCYRRHIZATE; CARBOMER; SOPHORA FLAVESCENS ROOT; COCOS NUCIFERA (COCONUT) OIL; PEG-100 STEARATE; AZELAIC ACID; HYDROXYACETOPHENONE; GLYCERYL STEARATE; OLDENLANDIA CAPENSIS WHOLE; ALLANTOIN; PANTHENOL; CETEARYL ALCOHOL; SODIUM ACRYLATE; PROPYLENE GLYCOL

Initial Drug Listing - AOSORW Folliculitis & Acne Treatment Cream

ACTIVE INGREDIENT

Salicylic Acid 1%

PURPOSE

Acne Treatment

INDICATIONS AND USAGE

- For the treatment of acne
- Helps prevent newacne blemishes

WARNINGS

For external use only

ASK DOCTOR

lf you are under 2 years of age.

WHEN USING

- Skin irritation and dryness are morelikely to occur when using another topical acne product at thesame time. lf irritation occurs, use only one product at a time
- Avoid eye area. In case of eye contact, flush gently and thoroughlywith water

KEEP OUT OF REACH OF CHILDREN

lf swallowed, get medical helpor contact the Poison Control Center right away

DOSAGE AND ADMINISTRATION

- Clean the skin thoroughly before applying this product.
- Cover the entire affected area with a thin layer one to threetimes daily.
- Because excessive drying of the skin may occur,start with one application daily, then gradually increase to two or three daily if needed or as directed by a doctor.
- lf bothersome dryness or peeling occurs, reduce application to once a day or every other day.
- Test for a New User. Apply product sparingly to one or two small affected areas during the first 3 days. lf no discomfort occurs, follow the directions stated elsewhere on this label.

OTHER SAFETY INFORMATION

Store at room temperature and out of direct sunlight. Keep the cap tightly closed after use。

INACTIVE INGREDIENT

Water, Glycerin, Cetearyl Alcohol, Propylene Glycol,Dimethicone,Sophora Flavescens Extract, Butyrospermum, Parkii (Shea) Butter, Cocos Nucifera (Coconut) Oil, Oldenlandia Diffusa Extract, PEG-100 Stearate, Dextrin, 1,2-HexanediolAloe Barbadensis Leaf Juice, Hydroxyacetophenone, CetearylGlucoside, Glyceryl Stearate, Panthenol, Triethanolamine Polyacrylate Crosspolymer-6, Carbomer, Allantoin, Niacinamide.Sodium Acrylate/Sodium Acryloyldimethyl Taurate Copolymer,Tocopheryl Acetate, Dipotassium Glycyrrhizate, Avena Sativa(Oat)Kernel Oil, Melaleuca Alternifolia (Tea Tree) Leaf Oil, Azelaic Acid, Ceramide NP

QUESTIONS

Visit www.aosorw.com